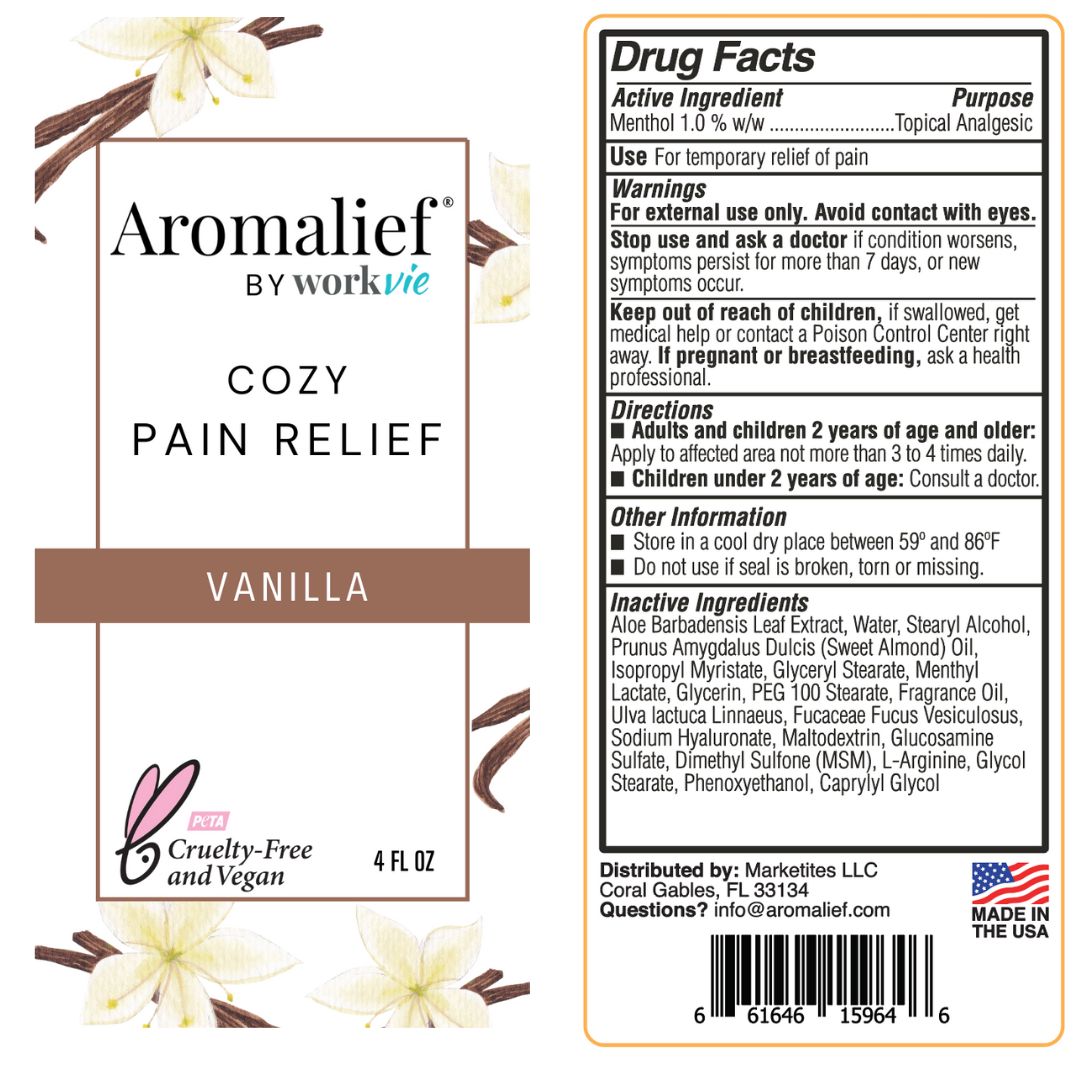 DRUG LABEL: Aromalief Cozy Vanilla Pain Relief Cream
NDC: 72393-303 | Form: LOTION
Manufacturer: Marketites LLC
Category: otc | Type: HUMAN OTC DRUG LABEL
Date: 20251029

ACTIVE INGREDIENTS: MENTHOL 1 g/100 g
INACTIVE INGREDIENTS: ISOPROPYL MYRISTATE; GLYCERYL STEARATE SE; ALMOND OIL; PEG-100 STEARATE; FUCUS VESICULOSUS; GLUCOSAMINE SULFATE; MENTHYL LACTATE, (-)-; GLYCERIN; DIMETHYL SULFONE; STEARYL ALCOHOL; ARGININE; CAPRYLYL GLYCOL; GLYCOL STEARATE; PHENOXYETHANOL; HYALURONATE SODIUM; MALTODEXTRIN; WATER; ULVA LACTUCA; ALOE VERA LEAF; FRAGRANCE 13576

Vanilla 4oz

Active Ingredients

Menthol 1.0% w/w

PURPOSE

Topical Analgesic

INDICATIONS AND USAGE

Use For temporary relief of pain

Warnings

For external use only. Avoid contact with eyes.

Stop use and ask a doctor if condition worsens, symptoms persist for more than 7 days, or new symptoms occur.

Keep out of reach of children, if swallowed, get medical help or contact a Poison Control Center right away. If pregnant or breastfeeding, ask a health professional.

Directions

Adults and children 2 years of age and older: Apply to affected area not more than 3 to 4 times daily. Children under 2 years of age: consult a doctor.

Ohter Information

Store in a cool dry place between 68º and 77ºF and relative humidity not exceeding 65%.

Do not use if seal is broken, torn or missing.

Inactive Ingredients

Aloe Barbadensis Leaf Extract, Water, Stearyl Alcohol, Prunus Amygdalus Dulcis (Sweet Almond) Oil, Isopropyl Myristate, Glyceryl Stearate, Menthyl Lactate, Glycerin, PEG 100 Stearate, Cannabis Sativa Seed Oil, Ulva lactuca Linnaeus, Fucaceae Fucus Vesiculosus, Sodium Hyaluronate, Helianthus Annuus (Sunflower) Seed Oil, Fragrance, Lavandula Angustifolia (Lavender) Flower Oil, Maltodextrin, Glucosamine Sulfate, Dimethyl Sulfone (MSM), L-Arginine, Glycol Stearate, Phenoxyethanol, Caprylyl Glycol

Questions

Distributed by Marketites LLC

Coral Gables, FL 33134

Made in the USA

Questions? info@aromalief.com